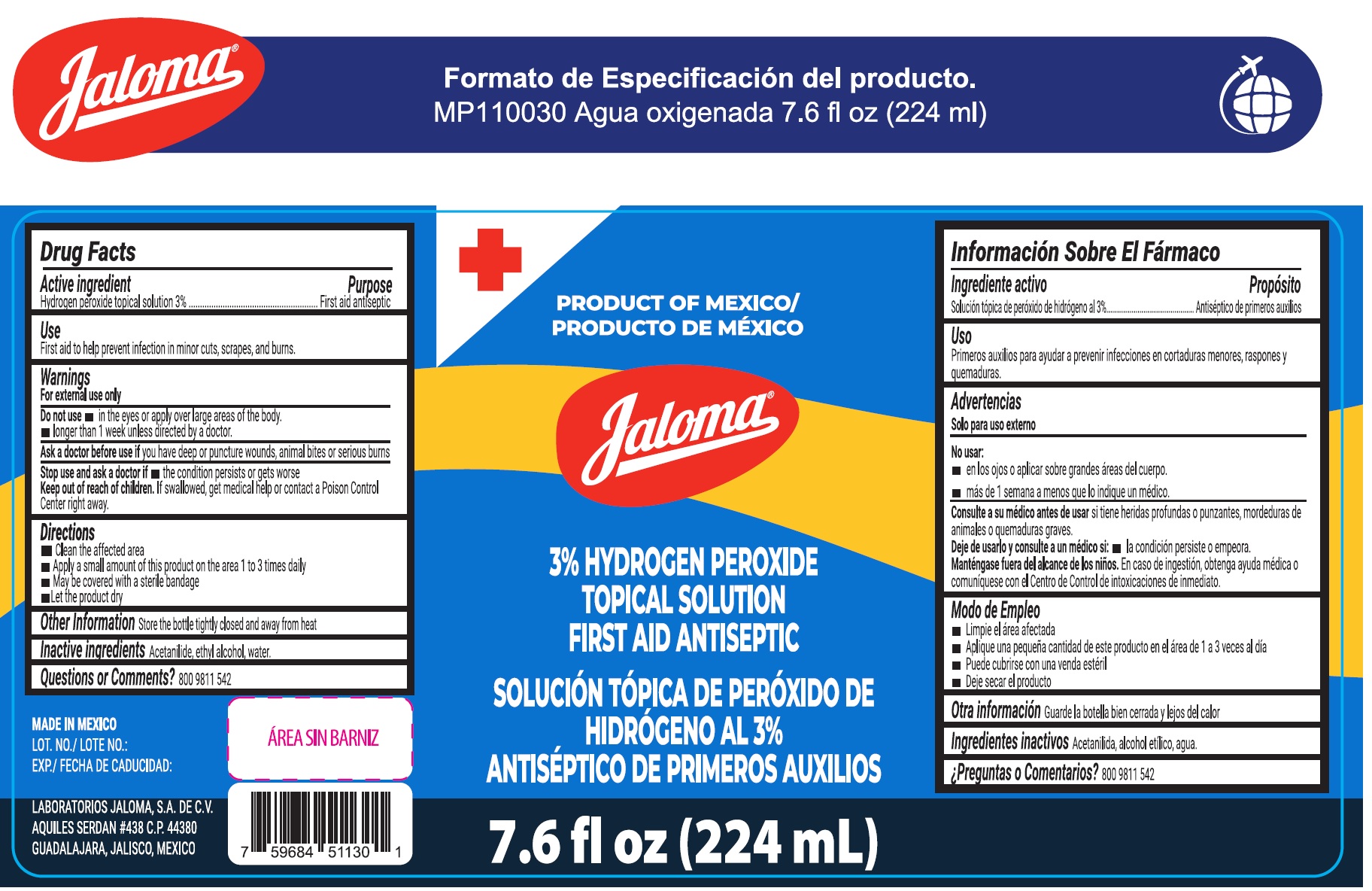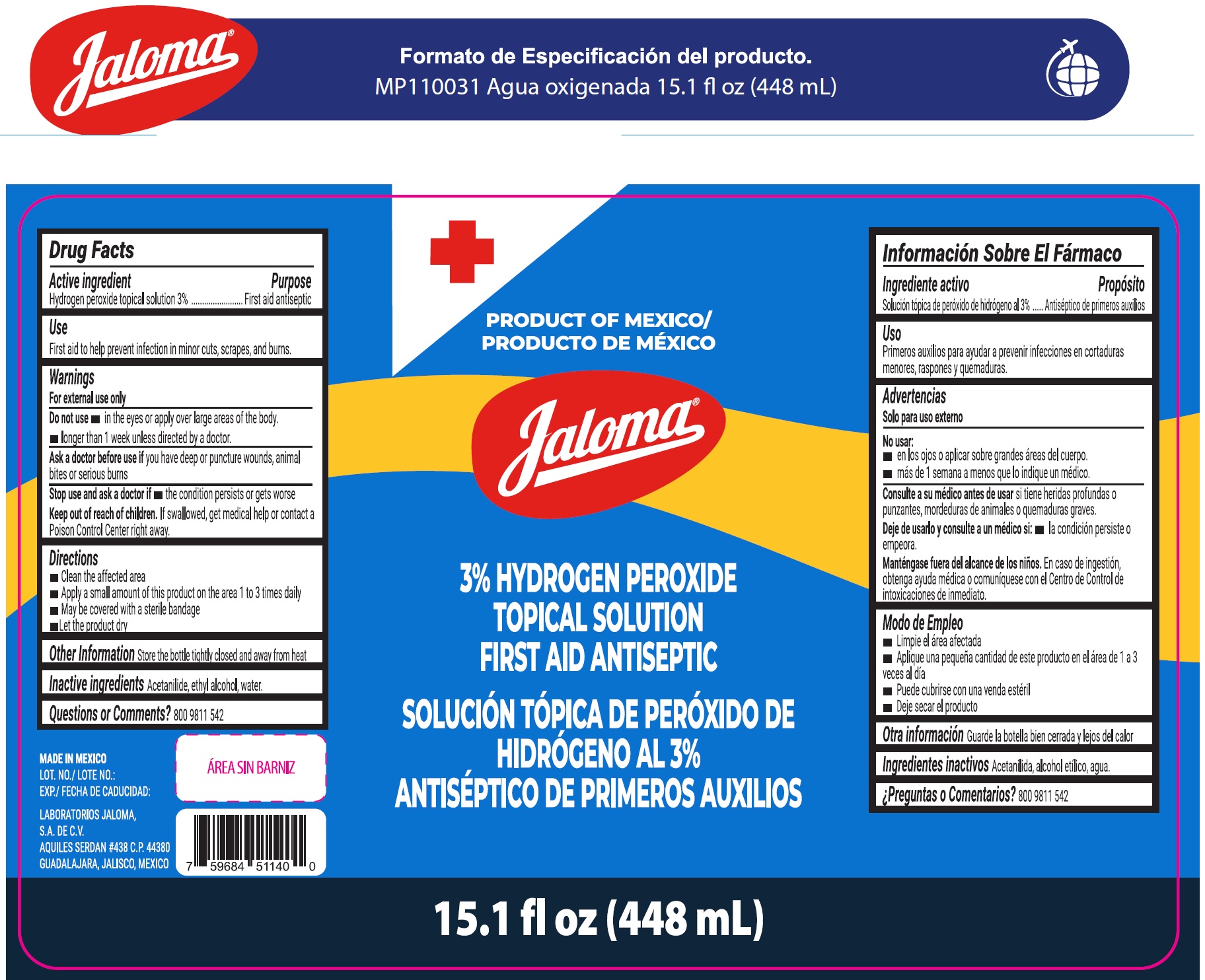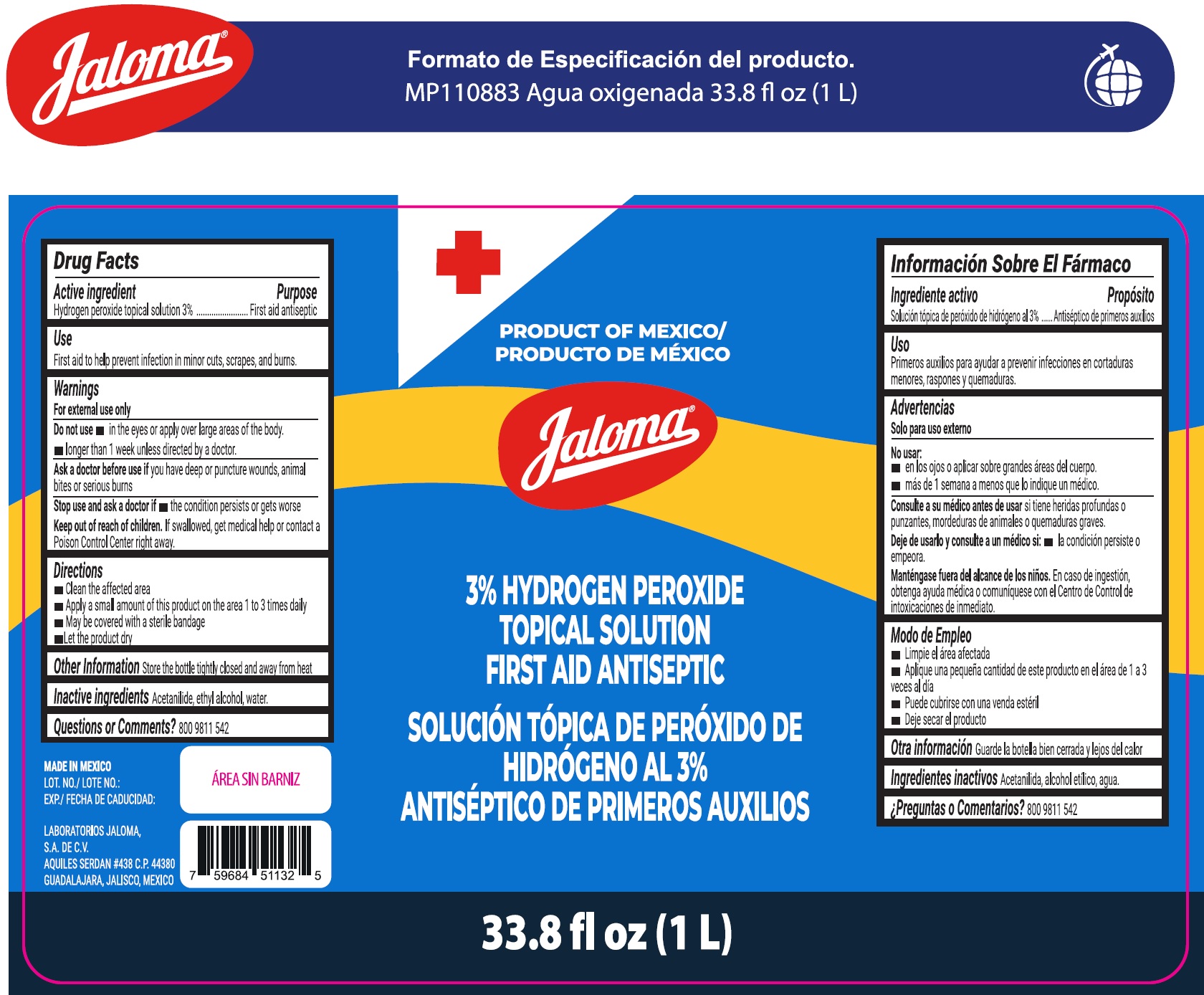 DRUG LABEL: Hydrogen Peroxide
NDC: 65055-501 | Form: SOLUTION
Manufacturer: Laboratorios Jaloma, S.A. de C.V.
Category: otc | Type: HUMAN OTC DRUG LABEL
Date: 20231109

ACTIVE INGREDIENTS: HYDROGEN PEROXIDE 30 mg/1 mL
INACTIVE INGREDIENTS: ACETANILIDE; ALCOHOL; WATER

Drug Facts

Active Ingredient

Hydrogen peroxide topical solution 3%

Purpose

First aid antiseptic

Use

First aid to help prevent infection in minor cuts, scrapes, and burns.

Warnings

For external use only

Do not use

• in the eyes or apply over large areas of the body.

• longer than 1 week unless directed by a doctor.

Ask a doctor before use if

you have deep or puncture wounds, animal bites or serious burns

Stop use and ask a doctor if

• the condition persists or gets worse

Keep out of the reach of children.

If swallowed, get medical help or contact a Poison Control Center right away.

Directions

• Clean the affected area

• Apply a small amount of this product on the area 1 to 3 times daily

• May be covered with a sterile bandage

• Let the product dry

Other Information

Store the bottle tightly closed and away from heat.

Inactive ingredients

Acetanilide, ethyl alcohol, water.

Questions or Comments?

800 9811 542